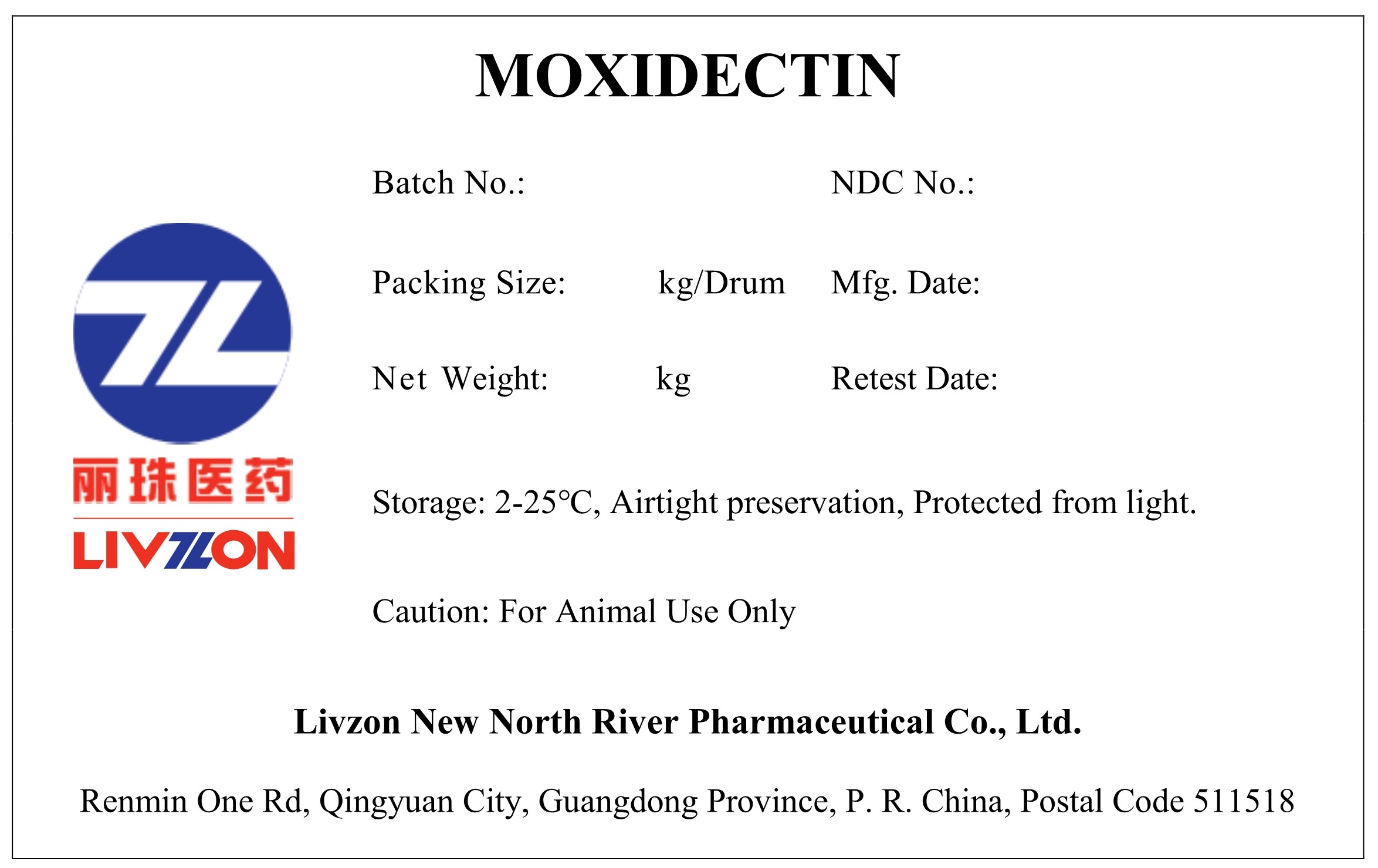 DRUG LABEL: Moxidectin
NDC: 20076-1235 | Form: POWDER
Manufacturer: Livzon New North River Pharmaceutical Co., Ltd.
Category: other | Type: BULK INGREDIENT - ANIMAL DRUG
Date: 20241224

ACTIVE INGREDIENTS: MOXIDECTIN 1 kg/1 kg

Moxidectin